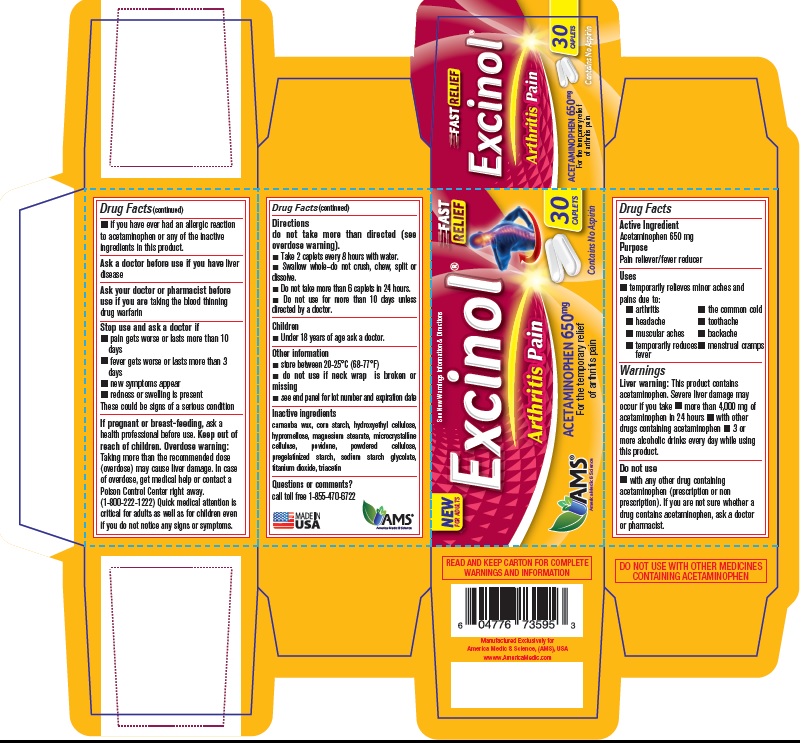 DRUG LABEL: Excinol Arthritis (Acetaminophen)
NDC: 49638-103 | Form: TABLET, DELAYED RELEASE
Manufacturer: America Medic & Science, LLC
Category: otc | Type: HUMAN OTC DRUG LABEL
Date: 20190122

ACTIVE INGREDIENTS: ACETAMINOPHEN 650 mg/1 1
INACTIVE INGREDIENTS: CARNAUBA WAX; HYDROXYETHYL CELLULOSE (100 MPA.S AT 2%); HYPROMELLOSE, UNSPECIFIED; MAGNESIUM STEARATE; MICROCRYSTALLINE CELLULOSE; POVIDONE; POWDERED CELLULOSE; STARCH, CORN; SODIUM STARCH GLYCOLATE TYPE A CORN; TITANIUM DIOXIDE; TRIACETIN

Excinol Arthritis (Acetaminophen) 650 mg

Excinol Arthritis (Acetaminophen) 650 mg

Drug Facts

Active Ingredient

Acetaminophen 650 mg

Purpose

Pain reliever/fever reducer

Uses

- temporarily relieves minor aches and pains due to:
- arthritis
- headache
- muscular aches
- temporarily reduces fever
- the common cold
- toothache
- backache
- menstrual cramps

Warnings

Liver warning: This product contains acetaminophen. Severe liver damage may occur if you take

- more than 4,000 mg of acetaminophen in 24 hours
- with other drugs containing acetaminophen
- 3 or more alcoholic drinks every day while using this product.

Do not use

- with any other drug containing acetaminophen (prescription or non prescription). If you are not sure whether a drug contains acetaminophen, ask a doctor or pharmacist.
- if you have ever had an allergic reaction to acetaminophen or any of the inactive ingredients in this product.

Ask a doctor before use if you have liver disease

ASK DOCTOR/PHARMACIST

Ask your doctor or pharmacist before use if you are taking the blood thinning drug warfarin

Stop use and ask a doctor if

- pain gets worse or lasts more than 10 days
- fever gets worse or lasts more than 3 days
- new symptoms appear
- redness or swelling is present

These could be signs of a serious condition

PREGNANCY OR BREAST FEEDING

If pregnant or breast-feeding, ask a health professional before use.

Keep out of reach of children.

Overdose warning

Overdose warning: Taking more than the recommended dose (overdose) may cause liver damage. In case of overdose, get medical help or contact a Poison Control Center right away. (1-800-222-1222) Quick medical attention is critical for adults as well as for children even if you do not notice any signs or symptoms.

Directions

do not take more than directed (see overdose warning).

- take 2 caplets every 8 hours with water.
- Swallow whole—do not crush, chew, split or dissolve.
- Do not take more than 6 caplets in 24 hours.
- Do not use for more than 10 days unless directed by a doctor.

Children

- Under 18 years of age ask a doctor.

Other information

- store between 20-25°C (68-77°F)
- do not use if neck wrap is broken or missing
- see end panel for lot number and expiration date

Inactive ingredients

- carnauba wax, corn starch, hydroxyethyl cellulose, hypromellose, magnesium stearate, microcrystalline cellulose, povidone, powdered cellulose, pregelatinized starch, sodium starch glycolate, titanium dioxide, triacetin

Questions or comments?

call toll free 1-855-470-6722